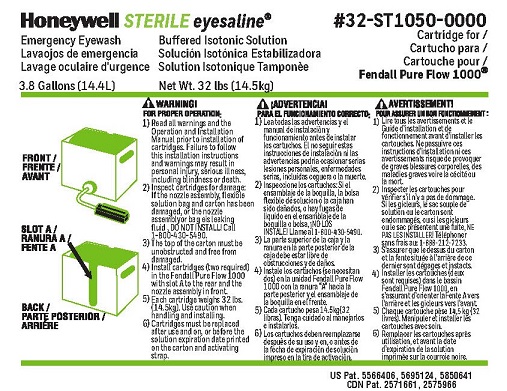 DRUG LABEL: Honeywell Sterile Eyesaline
NDC: 64809-103 | Form: LIQUID
Manufacturer: Sperian Eye & Face Protection Inc
Category: otc | Type: HUMAN OTC DRUG LABEL
Date: 20180619

ACTIVE INGREDIENTS: WATER 990 mL/1 L
INACTIVE INGREDIENTS: SODIUM PHOSPHATE, DIBASIC; SODIUM CHLORIDE; SODIUM PHOSPHATE, MONOBASIC

Sperian Eyesaline Emergency Eyewash

Drug Facts

Active Ingredient

Sterile water 99%

Purpose

Emergency Eyewash

Uses

For flushing the eye to reduce chances of severe injury caused by acid, alkali, or particulate contamination.

Warnings

For external use only

Do not use

- for injection
- in intraocular surgery
- internally

Ask a doctor before use if you have

- eye pain
- changes in vision
- redness or irritation of the eye after use
- an injury caused by alkali

Keep out of reach of children. If swallowed, get medical help or contact a Poison Control Center right away.

Directions

- do not dilute solution or reuse cartridge
- pull handle on the activating door to initiate flow
- lower head into flow for a minimum of 20 minutes
- continue flushing with water if necessary
- obtain medical treatment

Other information

- store at room temperature 59° to 86° F(15° to 30°C)
- do not freeze

Inactive ingredients

sodium chloride, sodium phosphate dibasic, sodium phosphate monobasic

Questions?

call 1-800 - 430-5490

Sperian Eye and Face Protection, Inc. (a Honeywell Company)

825 East Highway 151
Platteville, WI 53818

WARNING!

FOR PROPER OPERATION:

1. Read all warnings and the Operation and Installation Manual prior to installation of cartridges. Failure to follow this installation instructions and warnings may result in personal injury, serious illness, including blindness or death.
2. Inspect cartridges for damage: If the nozzle assembly, flexible soluton bag and carton has been damaged, or the nozzle assembly or bag is leaking fluid, DO NOT INSTALL! Call 1-800-430-5490.
3. The top of the carton must be unobstructed and free from damaged.
4. Install cartridges (two required) in the Fendall Pure Flow 1000 with slot A to the rear and theh nozzle assembly in front.
5. Each cartridge weighs 32 lbs (14.5 kg). Use caution when handling and installing.
6. Cartridges must be replaced after use and on, or before the solution expiration date printed on the carton and activating strap.

PACKAGE LABEL

Honeywell STERILE eyesaline®

Emergency Eyewash

Buffered Isotonic Solution

3.9 Gallons (14.4L)

Net Wt. 32 lbs (14.5kg)